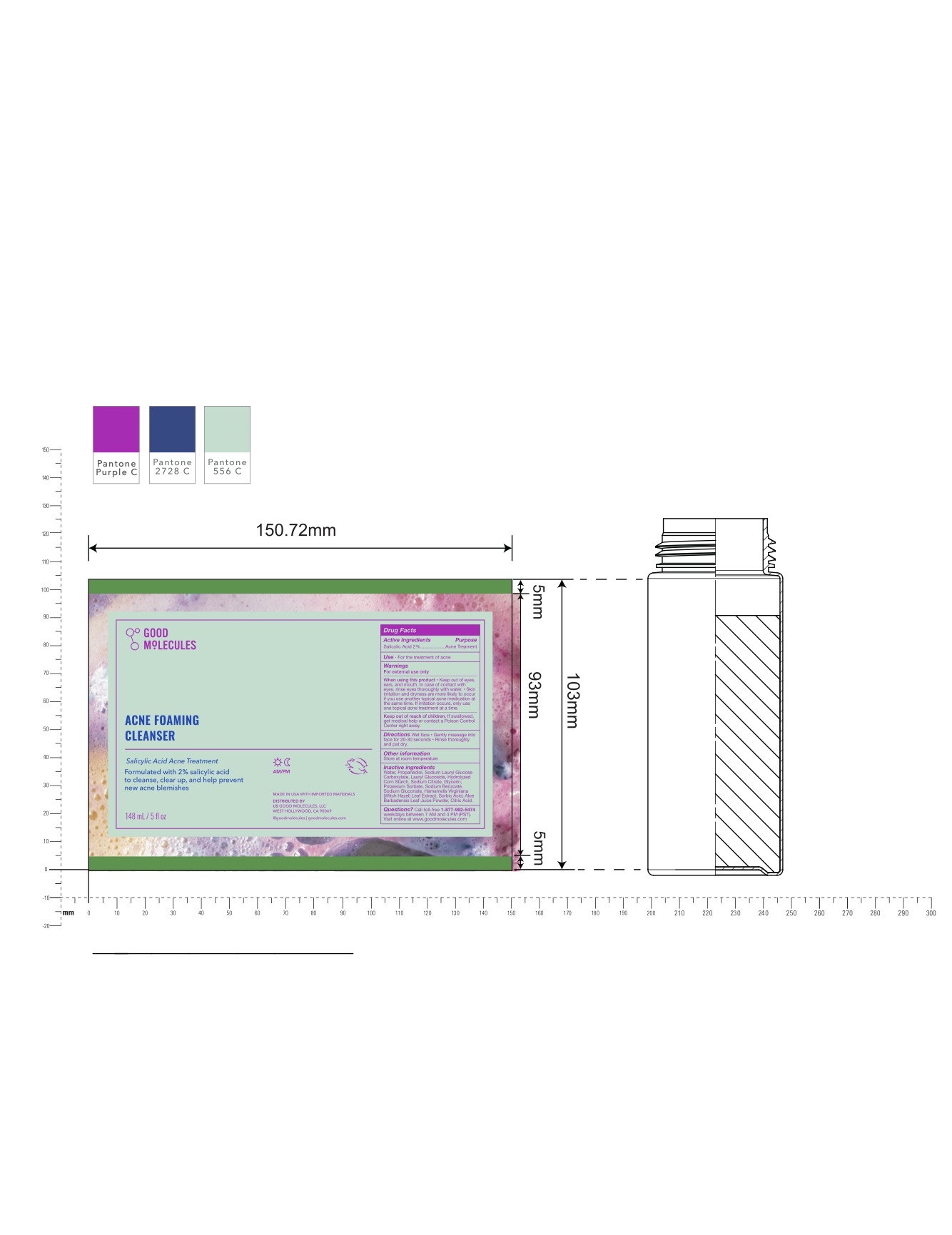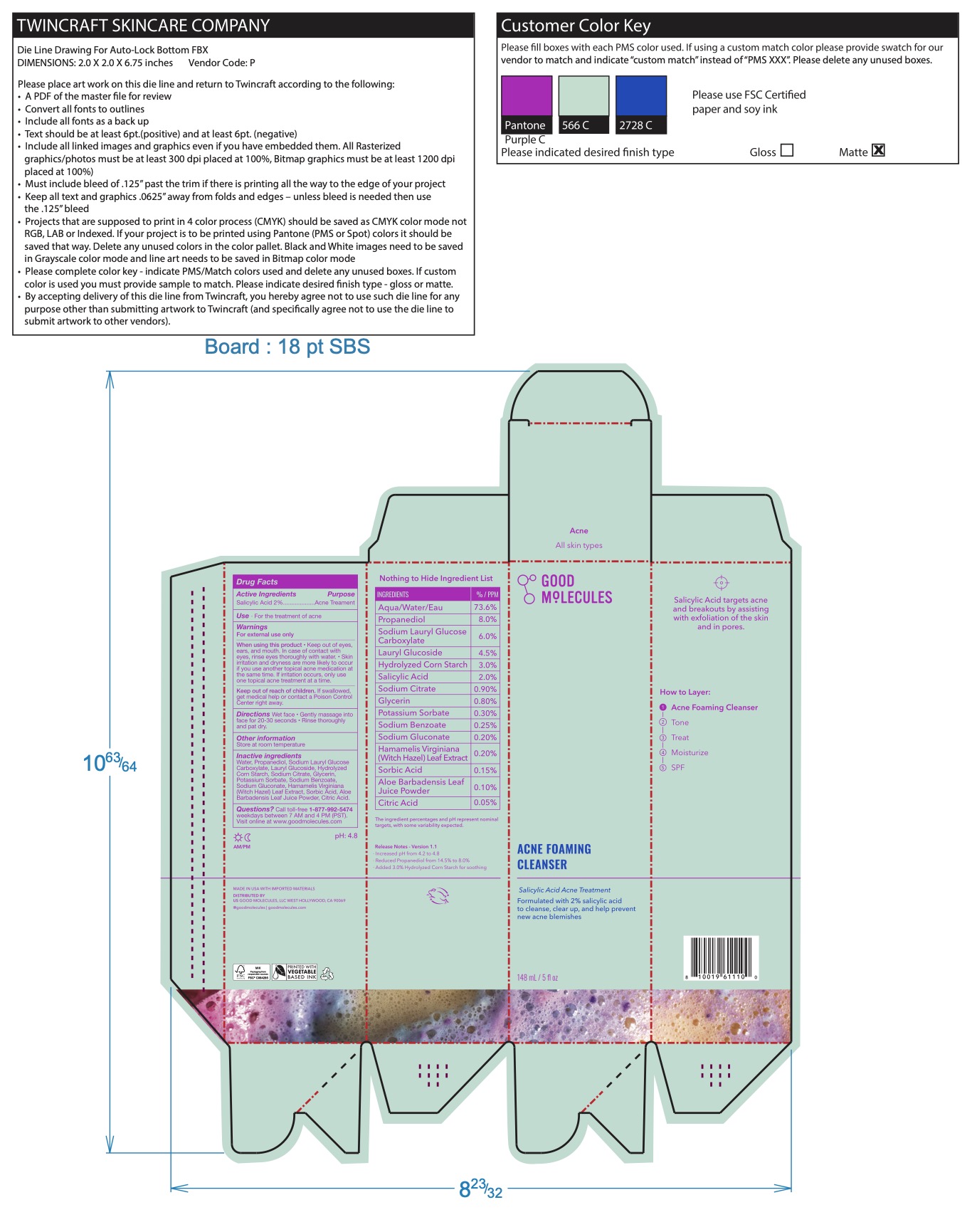 DRUG LABEL: Good Molecules Acne Foaming Cleanser
NDC: 64412-1005 | Form: GEL
Manufacturer: Twincraft Inc.
Category: otc | Type: HUMAN OTC DRUG LABEL
Date: 20260123

ACTIVE INGREDIENTS: SALICYLIC ACID 2 g/100 mL
INACTIVE INGREDIENTS: SODIUM LAURYL GLYCOL CARBOXYLATE; CORN SYRUP; PROPANEDIOL; GLYCERIN; SODIUM BENZOATE; ALOE VERA LEAF; SODIUM CITRATE; SODIUM GLUCONATE; LAURYL GLUCOSIDE; POTASSIUM SORBATE; SORBIC ACID; WATER; HAMAMELIS VIRGINIANA LEAF; ANHYDROUS CITRIC ACID

Purpose

Acne treatment

Use

For the treatment of acne

Active Ingredient

Salicylic Acid 2%

Directions

Wet face

- Gently massage into face for 20-30 seconds
- Rinse thoroughly and pat dry.

WARNINGS

For external use only

Keep out of reach of children

If swallowed, get medical help or contact a Poison Control Center right away

When using this product

- Keep out of eyes, ears, and mouth. In case of contact with eyes, rinse eyes thoroughly with water.
- Skin irritation and dryness are more likely to occur if you use another topical acne medication at the same time. If irritation occurs, only use one topical acne treatment at a time.

Inactive Ingredients

Water, Propanediol, Sodium Lauryl Glucose Carboxylate, Lauryl Glucoside, Hydrolyzed Corn Starch, Sodium Citrate, Glycerin, Potassium Sorbate, Sodium Benzoate, Sodium Gluconate, Hamamelis Virginiana (Witch Hazel) Leaf Extract, Sorbic Acid, Aloe Barbadensis Leaf Juice Powder, Citric Acid.

Other Information

Store at room temperature

Questions?

Call toll-free 1-877-992-5474weekdays between 7 AM and 4 PM (PST). Visit online at www.goodmolecules.com